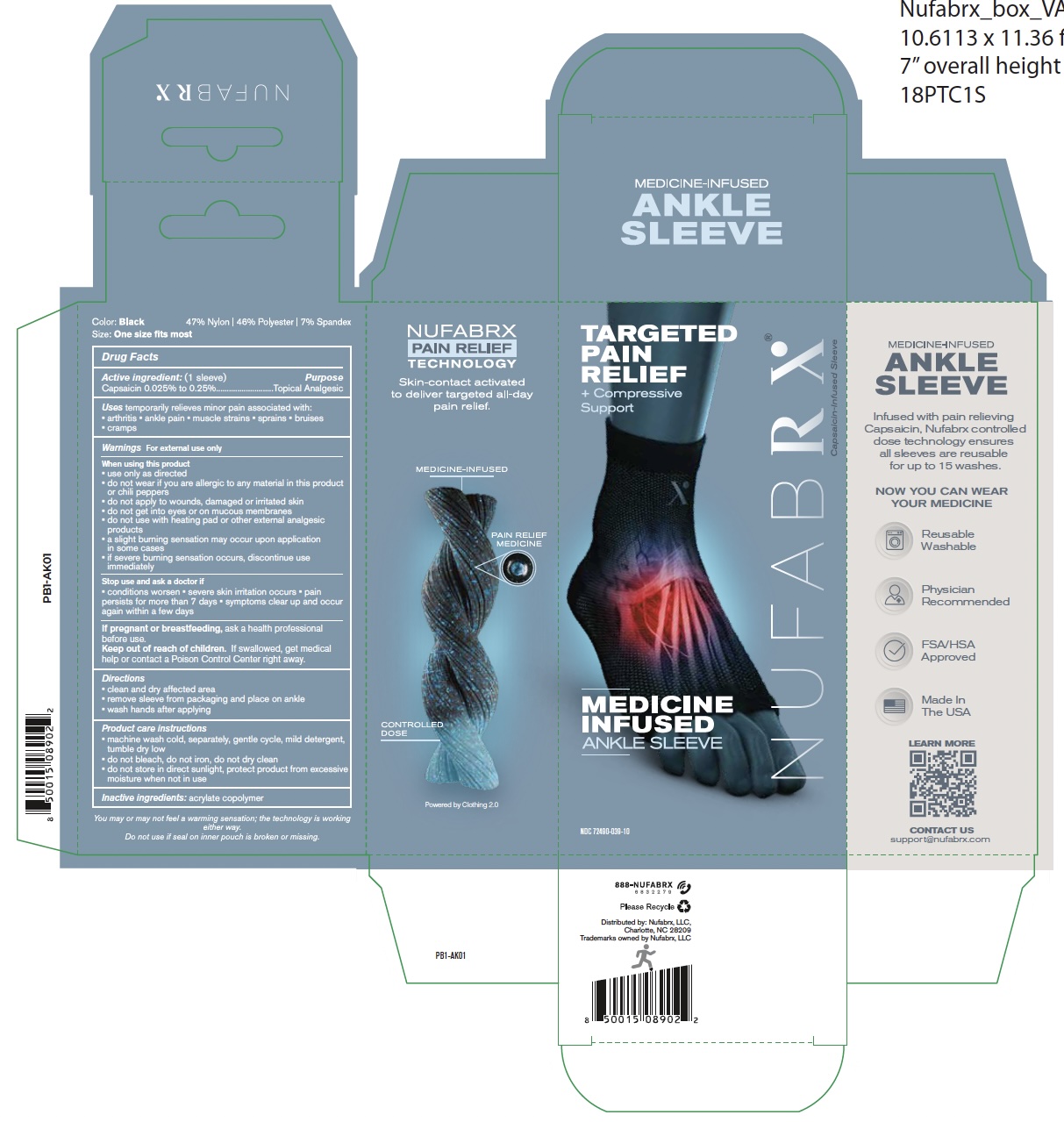 DRUG LABEL: Nufabrx Medicine Infused Ankle Sleeve
NDC: 72490-039 | Form: CLOTH
Manufacturer: Nufabrx LLC
Category: otc | Type: HUMAN OTC DRUG LABEL
Date: 20251015

ACTIVE INGREDIENTS: CAPSAICIN 0.25 g/100 g
INACTIVE INGREDIENTS: BUTYL ACRYLATE/METHYL METHACRYLATE/METHACRYLIC ACID COPOLYMER (18000 MW)

72490-039 Nufabrx Ankle Sleeve

Active ingredient

Capsaicin 0.25% to 0.25%

Purpose

Topical Analgesic

Uses

Temporary relieves minor pain associated with:

- arthritis
- ankle pain
- muscle strains
- sprains
- bruises
- cramps

Directions

- clean and dry affected area
- remove sleeve from packaging and place on ankle
- wash hands after applying

Product care instructions

- machine wash cold, separately, gentle cycle, mild detergent, tumble dry low
- do not bleach, do not iron, do not dry clean
- do not store in direct sublight, protect product from excessive moisture when not in use

Inactive ingredient

acrylate copolymer

Directions

Replaced to use 10 hours maximum with wash hands after applying

Warnings

For external use only.

Stop use and ask a doctor if

- conditions worsen
- severe skin irritation occurs
- pain persists for more than 7 days
- symptoms clear up and occur again within a few days

If pregnant or breast-feeding

Ask a health professional before use.

Keep out of reach children

If swallowed, get medical help or contact a Poison Control Center right away.

When using this product

- use only as directed
- do not wear if you are allergic to any material in this product or chili peppers
- do not apply to wounds, damaged or irritated skin
- do not get into eyes or on mucous membranes
- do not use with heating pad or other external analgesic products
- a slight burning sensation may occur upon application in some cases
- if severe burning sensation occurs, discontinue use immediately